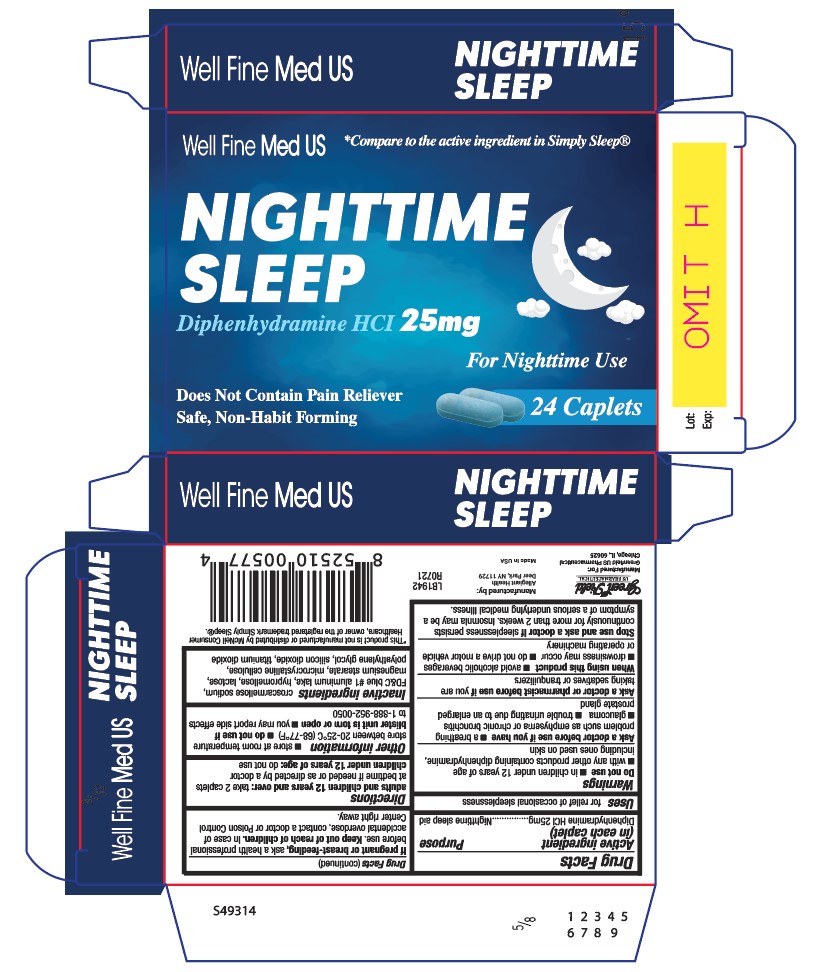 DRUG LABEL: Diphenhydramine HCl 25mg
NDC: 69168-002 | Form: TABLET, COATED
Manufacturer: Allegiant Health
Category: otc | Type: HUMAN OTC DRUG LABEL
Date: 20211123

ACTIVE INGREDIENTS: DIPHENHYDRAMINE HYDROCHLORIDE 25 mg/1 1
INACTIVE INGREDIENTS: CROSCARMELLOSE SODIUM; FD&C BLUE NO. 1 ALUMINUM LAKE; HYPROMELLOSE, UNSPECIFIED; LACTOSE, UNSPECIFIED FORM; MAGNESIUM STEARATE; MICROCRYSTALLINE CELLULOSE; POLYETHYLENE GLYCOL, UNSPECIFIED; SILICON DIOXIDE; TITANIUM DIOXIDE

GreenField - Sleep Aid

Active ingredient(s)

Diphenhydramine HCl 25 mg

Purpose

Nighttime sleep aid

Use(s)

for relief of occasional sleeplessness

Warnings

Do not use

- In children under 12 years of age
- With any other product containing diphenydramine, even one used on skin

Ask a doctor before use if

- a breathing problem such as emphysema or chronic bronchitis
- glaucoma
- trouble urinating due to an enlarged prostate gland

Ask a doctor or pharmacist before use if

you are taking sedatives or tranquilizers

When using this product

- avoid alcoholic beverages
- drowsiness will occur
- do not drive a motor vehicle or operate machinery

Stop use and ask a doctor if

sleeplessness persists continuously for more than 2 weeks. Insomnia may be a symptom of
a serious underlying medical illness.

Pregnancy/Breastfeeding

If pregnant or breast-feeding, ask a health professional before use.

Keep out of reach of children

In case of accidental overdose, contact a doctor or Poison Control Center right away.

Directions

adults and children 12 years and over: take 2 caplets at bedtime if needed or as directed by a doctor

children under 12 years of age: do not use

Other information

- store at room temperature 20°– 25°C (68°– 77°F)
- do not use if blister unit is torn or open
- you may report side effects to 1-888-952-0050

Inactive ingredients

croscarmellose sodium, FD&C blue #1 aluminum lake, hypromellose, lactose, magnesium
stearate, microcrystalline cellulose, polyethylene glycol, silicon dioxide, titanium dioxide

Principal Display Panel

Sleep Aid